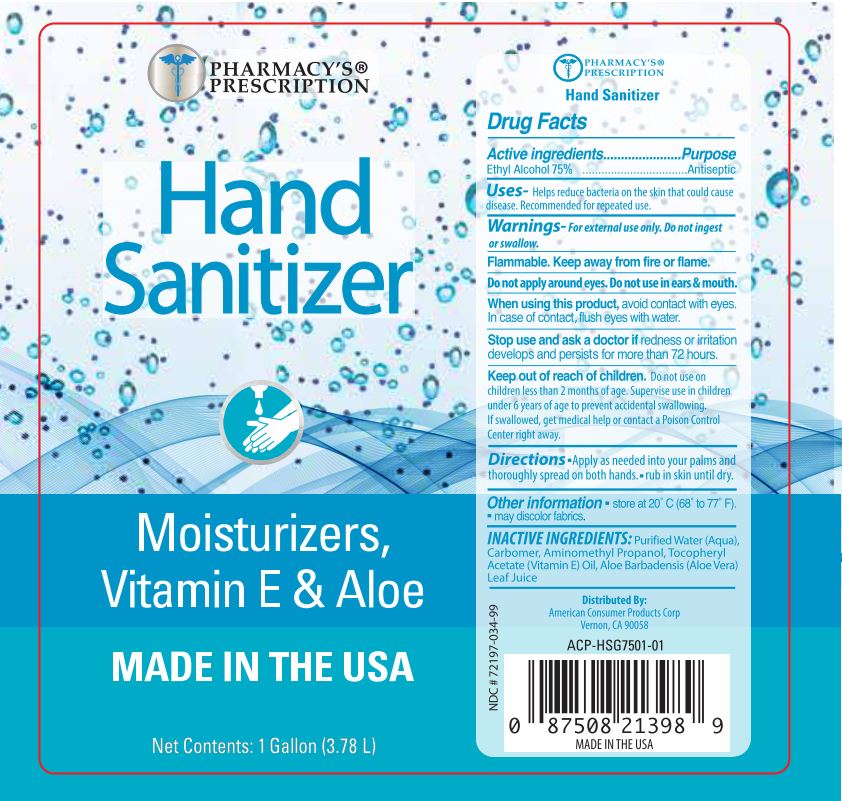 DRUG LABEL: Pharmacys Prescription Hand Sanitizer
NDC: 72197-034 | Form: GEL
Manufacturer: American Consumer Products Corp
Category: otc | Type: HUMAN OTC DRUG LABEL
Date: 20200814

ACTIVE INGREDIENTS: ALCOHOL 75 mL/100 mL
INACTIVE INGREDIENTS: CARBOMER HOMOPOLYMER, UNSPECIFIED TYPE; ALOE VERA LEAF; WATER; AMINOMETHYLPROPANOL; .ALPHA.-TOCOPHEROL ACETATE

Pharmacys Prescription Hand Sanitizer

Active Ingredient

Active Ingredients - Ethyl Alcohol 75%

Purpose

Antiseptic

Uses

Uses - Helps reduce bacteria on the skin that could cause disease. Recommended for repeated use.

Warnings

Warnings - For external use only. Do not ingest or swallow.

Flammable. Keep away from fire or flame.

Do not appy around eyes. Do not use in ears & mouth.

When using this product, avoid contact with eyes. In case of contact, flush eyes with water.

Stop use and ask a doctor if redness or irritation develops and persists for more than 72 hours.

Keep out of reach of children. Do not use on children less than 2 months of age. Supervise use in children under 6 years of age to prevent accidental swallowing. If swallowed, get medical help or contact a Poison Control Center right away.

Directions

Directions - apply as needed into your palms and thoroughly spread on both hands. Rub into skin until dry.

Other information

Other information - store at 20º C (68º to 77º F). May discolor fabrics.

INACTIVE INGREDIENT

INACTIVE INGREDIENTS: Purified Water (Aqua), Carbomer, Aminomethyl Propanol, Tocopheryl Acetate (Vitamin E), Aloe Barbadensis (Aloe Vera) Leaf Juice